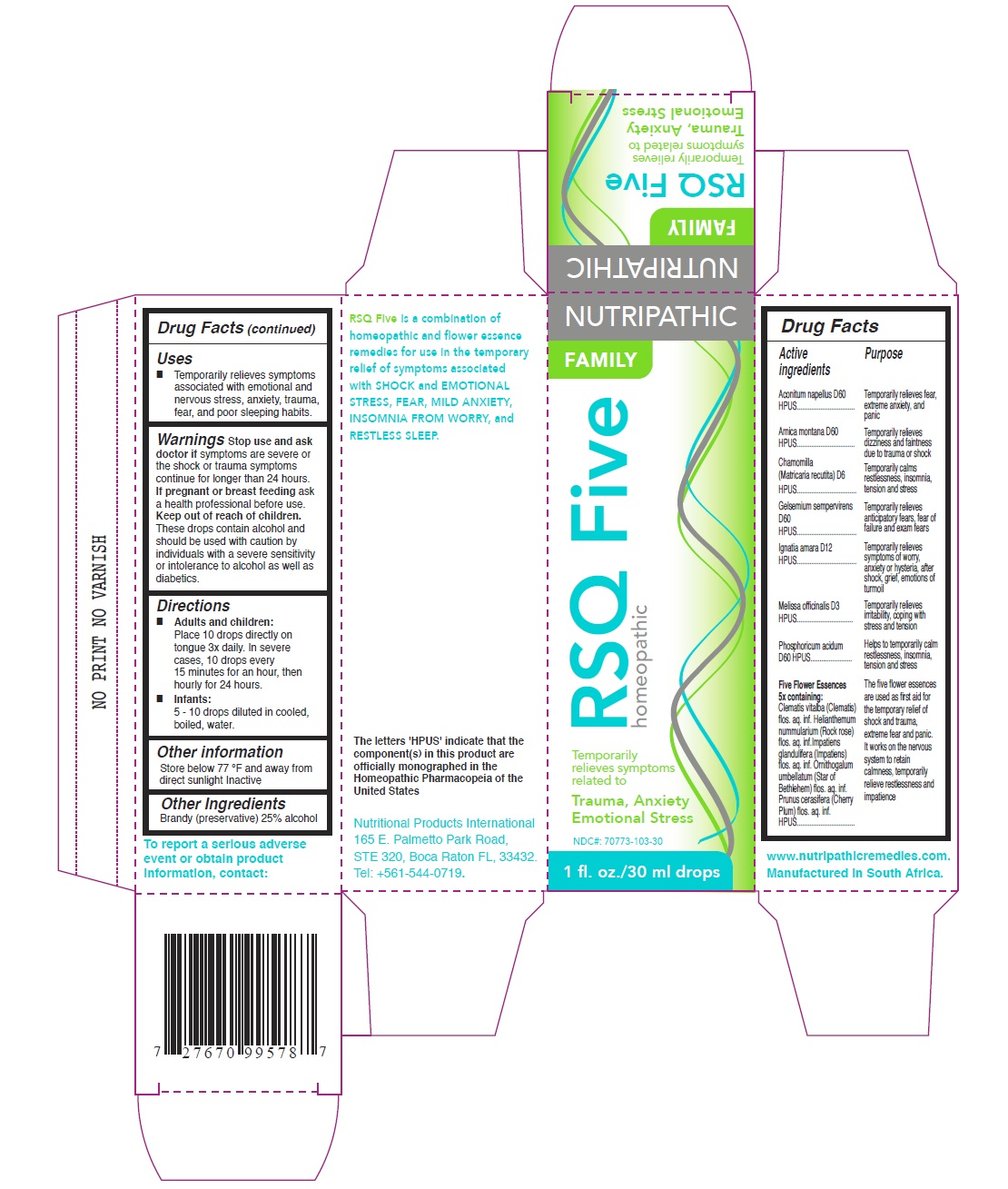 DRUG LABEL: RSQ FIVE
NDC: 70773-103 | Form: LIQUID
Manufacturer: PRIVATE LABEL BRANDS CC
Category: homeopathic | Type: HUMAN OTC DRUG LABEL
Date: 20171227

ACTIVE INGREDIENTS: PHOSPHORIC ACID 60 [hp_X]/100 [hp_X]; ACONITUM NAPELLUS 60 [hp_X]/100 [hp_X]; MATRICARIA CHAMOMILLA 6 [hp_X]/100 [hp_X]; ORNITHOGALUM UMBELLATUM FLOWERING TOP 5 [hp_X]/100 [hp_X]; IMPATIENS GLANDULIFERA FLOWER 5 [hp_X]/100 [hp_X]; ARNICA MONTANA 60 [hp_X]/100 [hp_X]; MELISSA OFFICINALIS 3 [hp_X]/100 [hp_X]; PRUNUS CERASIFERA FLOWER 5 [hp_X]/100 [hp_X]; GELSEMIUM SEMPERVIRENS WHOLE 60 [hp_X]/100 [hp_X]; STRYCHNOS IGNATII SEED 12 [hp_X]/100 [hp_X]; HELIANTHEMUM NUMMULARIUM FLOWER 5 [hp_X]/100 [hp_X]; CLEMATIS VITALBA FLOWER 5 [hp_X]/100 [hp_X]
INACTIVE INGREDIENTS: ALCOHOL

ACTIVE INGREDIENTS (OTC-ACTIVE INGREDIENT SECTION)

Aconitum napellus D60 HPUS

Arnica montana D60 HPUS

Chamomilla (Matricaria recutita) D6 HPUS

Gelsemium sempervirens D60 HPUS

Ignatia amara D12 HPUS

Melissa officinalis D3 HPUS

Phosphoricum acidum D60 HPUS

Five Flower Essences 5x containing:

Clematis vitalba (Clematis) flos. aq. inf.

Helianthemum nummularium (Rock rose) flos. aq. inf.

Impatiens glandulifera (Impatiens) flos. aq. inf.

Ornithogalum umbellatum (Star of Bethlehem) flos. aq. inf.

Prunus cerasifera (Cherry Plum) flos. aq. inf. HPUS

PURPOSE (DOSAGE & ADMINISTRATION SECTION)

Temporarily relieves fear, extreme anxiety, and panic

Temporarily relieves dizziness and faintness due to trauma or shock

Temporarily calms restlessness, insomnia, tension and stress

Temporarily relieves anticipatory fears, fear of failure and exam fears

Temporarily relieves symptoms of worry, anxiety or hysteria, after shock, grief, emotions of turmoil

Temporarily relieves irritability, coping with stress and tension

Helps to temporarily calm restlessness, insomnia, tension and stress

The five flower essences are used as first aid for the temporary relief of shock and trauma, extreme fear and panic.

It works on the nervous system to retain calmness, temporarily relieve restlessness and impatience

KEEP OUT OF REACH OF CHILDREN (KEEP OUT OF REACH OF CHILDREN SECTION)

KEEP OUT OF REACH OF CHILDREN

DIRECTIONS (INDICATIONS & USAGE SECTION)

Adults and children:

Place 10 drops directly on tongue 3x daily. In severe cases, 10 drops every 15 minutes for an hour, then hourly for 24 hours.

Infants:

5 - 10 drops diluted in cooled, boiled, water.

OTHER INFORMAITON (INSTRUCTIONS FOR USE SECTION)

Store below 77 °F and away from direct sunlight

WARNING (WARNINGS SECTION)

These drops contain alcohol and should be used with caution by individuals with a severe sensitivity or intolerance to alcohol as well as diabetics.

STOP USE AND ASK DOCTOR IF (OTC- STOP USE SECTION)

symptoms are severe or the shock or trauma symptoms continue for longer than 24 hours.

IF PREGNANT OR BREASTFEEDING, (OTC- PREGNANCY OR BREAST FEEDING SECTION)

ask a health professional before use.

INACTIVE INGREDIENTS (INACTIVE INGREDIENT SECTION)

Brandy (preservative) 25% alcohol